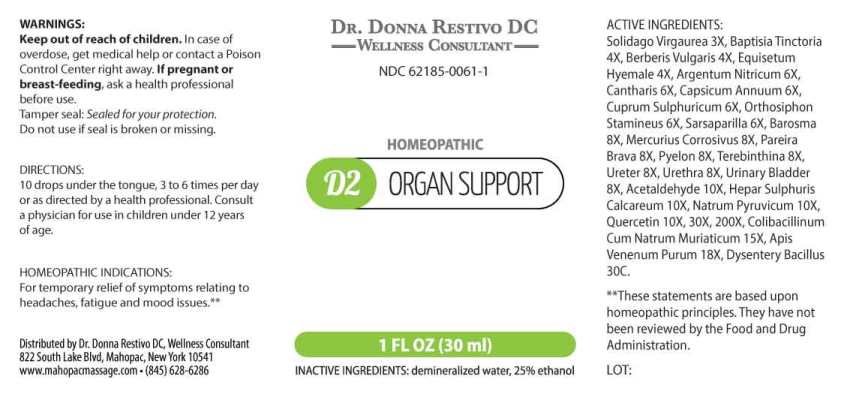 DRUG LABEL: D2 Organ Support
NDC: 62185-0061 | Form: LIQUID
Manufacturer: Dr. Donna Restivo DC
Category: homeopathic | Type: HUMAN OTC DRUG LABEL
Date: 20230110

ACTIVE INGREDIENTS: SOLIDAGO VIRGAUREA FLOWERING TOP 3 [hp_X]/1 mL; BAPTISIA TINCTORIA ROOT 4 [hp_X]/1 mL; BERBERIS VULGARIS ROOT BARK 4 [hp_X]/1 mL; EQUISETUM HYEMALE 4 [hp_X]/1 mL; SILVER NITRATE 6 [hp_X]/1 mL; LYTTA VESICATORIA 6 [hp_X]/1 mL; CAPSICUM 6 [hp_X]/1 mL; CUPRIC SULFATE 6 [hp_X]/1 mL; CLERODENDRANTHUS SPICATUS LEAF 6 [hp_X]/1 mL; SMILAX ORNATA ROOT 6 [hp_X]/1 mL; AGATHOSMA BETULINA LEAF 8 [hp_X]/1 mL; MERCURIC CHLORIDE 8 [hp_X]/1 mL; CHONDRODENDRON TOMENTOSUM ROOT 8 [hp_X]/1 mL; SUS SCROFA RENAL PELVIS 8 [hp_X]/1 mL; TURPENTINE OIL 8 [hp_X]/1 mL; SUS SCROFA URETER 8 [hp_X]/1 mL; SUS SCROFA URETHRA 8 [hp_X]/1 mL; SUS SCROFA URINARY BLADDER 8 [hp_X]/1 mL; ACETALDEHYDE 10 [hp_X]/1 mL; CALCIUM SULFIDE 10 [hp_X]/1 mL; SODIUM PYRUVATE 10 [hp_X]/1 mL; QUERCETIN 10 [hp_X]/1 mL; ESCHERICHIA COLI 15 [hp_X]/1 mL; APIS MELLIFERA VENOM 18 [hp_X]/1 mL; SHIGELLA DYSENTERIAE 30 [hp_C]/1 mL
INACTIVE INGREDIENTS: WATER; ALCOHOL

DRUG FACTS:

ACTIVE INGREDIENTS:

Solidago Virgaurea 3X, Baptisia Tinctoria 4X, Berberis Vulgaris 4X, Equisetum Hyemale 4X, Argentum Nitricum 6X, Cantharis 6X, Capsicum Annuum 6X, Cuprum Sulphuricum 6X, Orthosiphon Stamineus 6X, Sarsaparilla (Smilax Regelii) 6X, Barosma (Betulina) 8X, Mercurius Corrosivus 8X, Pareira Brava 8X, Pyelon (Suis) 8X, Terebinthina 8X, Ureter (Suis) 8X, Urethra (Suis) 8X, Urinary Bladder (Suis) 8X, Acetaldehyde 10X, Hepar Sulphuris Calcareum 10X, Natrum Pyruvicum 10X, Quercetin 10X, 30X, 200X, Colibacillinum Cum Natrum Muriaticum 15X, Apis Venenum Purum 18X, Dysentery Bacillus 30C.

HOMEOPATHIC INDICATIONS:

For temporary relief of symptoms relating to headaches, fatigue and mood issues.**

**These statements are based upon homeopathic principles. They have not been reviewed by the Food and Drug Administration.

WARNINGS:

Keep out of reach of children. In case of overdose, get medical help or contact a Poison Control Center right away.

If pregnant or breast-feeding, ask a health professional before use. Tamper seal: Sealed for your protection.

Do not use if seal is broken or missing.

Keep out of reach of children. In case of overdose, get medical help or contact a Poison Control Center right away.

DIRECTIONS:

10 drops under the tongue, 3 to 6 times a day or as directed by a health professional. Consult a physician for use in children under 12 years of age.

HOMEOPATHIC INDICATIONS:

For temporary relief of symptoms relating to headaches, fatigue and mood issues.**

**These statements are based upon homeopathic principles. They have not been reviewed by the Food and Drug Administration.

INACTIVE INGREDIENTS:

demineralized water, 25% ethanol

QUESTIONS:

Distributed by Dr. Donna Restivo DC, Wellness Consultant

822 South Lake Blvd. Mahopac, New York 10541

www.mahopacmassage.com • (845) 628-6286

PACKAGE LABEL DISPLAY:

DR. DONNA RESTIVO DC
WELLNESS CONSULTANT
NDC 62185-0061-1
HOMEOPATHIC
D2 ORGAN SUPPORT
1 FL OZ (30 ml)